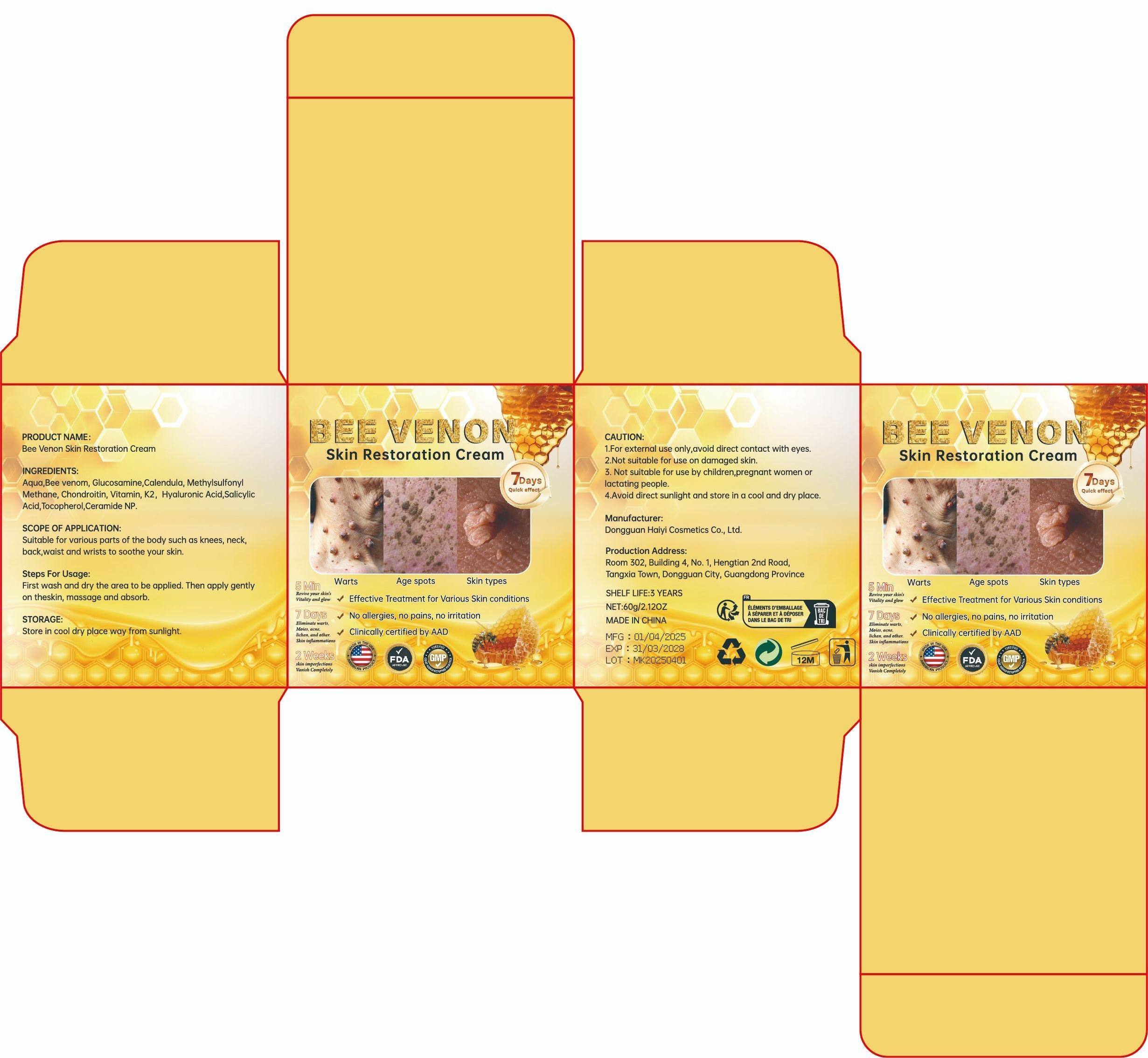 DRUG LABEL: BeeVenon Skin Restoration Cream
NDC: 85594-006 | Form: CREAM
Manufacturer: Dongguan Haiyi Cosmetics Co., Ltd.
Category: otc | Type: HUMAN OTC DRUG LABEL
Date: 20250711

ACTIVE INGREDIENTS: MELITTIN 6 mg/100 g
INACTIVE INGREDIENTS: HYALURONIC ACID; CHONDROSINE; TOCOPHEROL; DIMETHYL SULFONE; SALICYLIC ACID; MENAQUINONE 6; CALENDULA ARVENSIS LEAF; CERAMIDE NP; AQUA; GLUCOSAMINE

85594-006-01Bee Venon Skin Restoration Cream

ACTIVE INGREDIENT

Melittin

INACTIVE INGREDIENT

Aqua,Glucosamine,Calendula, Methylsulfonyl Methane, Chondroitin, Vitamin K2, Hyaluronic Acid,SalicylicAcid,Tocopherol,Ceramide NP.

PURPOSE

Effective Treatment for Various Skin conditions。（Warts，Age spots，Skin types）

WARNINGS

1.For external use only,avoid direct contact with eyes.

2.Not suitable for use on damaged skin.

3. Not suitable for use by children,pregnant women orlactating people.

4.Avoid direct sunlight and store in a cool and dry place.

STOP USE

This product may cause allergic reactions in asmall number of people.
lf youexperience any discomfort,please stop using it immediately.

DO NOT USE

Not suitable for use by children, pregnantor breast feeding people.

KEEP OUT OF REACH OF CHILDREN

KEEP THE PRODUCT OUT OF REACH OF CHILDREN to

INDICATIONS AND USAGE

First wash and dry the area to be applied. Then apply gentlyon theskin, massage and absorb.

DOSAGE AND ADMINISTRATION

5 Min
Revive your skin's Vitality and glow
7 Days
Eliminate warts,Moies, acne.

Hichen, and other.Skin inflammations
2 Weeks

skin imperfections Vartish Completely